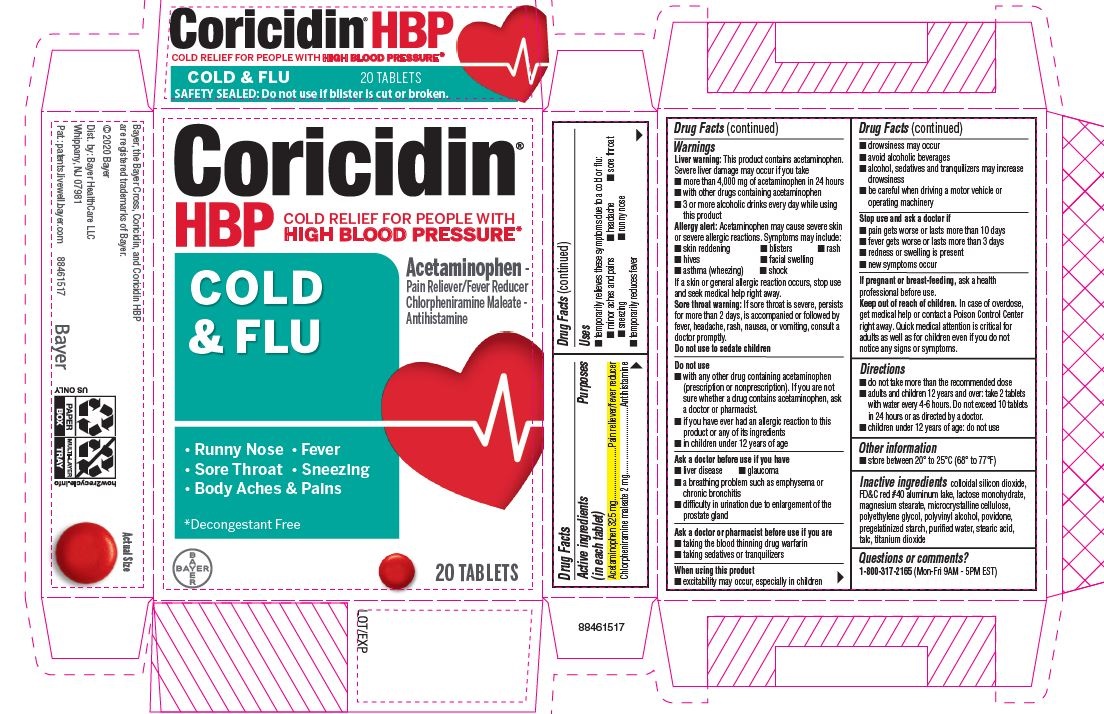 DRUG LABEL: Coricidin HBP
NDC: 11523-4325 | Form: TABLET, FILM COATED
Manufacturer: Bayer HealthCare LLC.
Category: otc | Type: HUMAN OTC DRUG LABEL
Date: 20250218

ACTIVE INGREDIENTS: ACETAMINOPHEN 325 mg/1 1; CHLORPHENIRAMINE MALEATE 2 mg/1 1
INACTIVE INGREDIENTS: LACTOSE MONOHYDRATE; STARCH, CORN; FD&C RED NO. 40; ALUMINUM OXIDE; ANHYDROUS LACTOSE; MAGNESIUM STEARATE; CELLULOSE, MICROCRYSTALLINE; POLYETHYLENE GLYCOL, UNSPECIFIED; POLYVINYL ALCOHOL; POVIDONE; TALC; TITANIUM DIOXIDE

Coricidin® HBP Cold & Flu

Drug Facts

ACTIVE INGREDIENT

Active ingredients (in each tablet) | Purpose
Acetaminophen 325 mg | Pain reliever/ fever reducer
Chlorpheniramine maleate 2 mg | Antihistamine

Uses

- temporarily relieves
  - minor aches and pains
  - headache
  - sneezing
  - runny nose
- temporarily reduces fever

Warnings

Liver Warning

This product contains acetaminophen. Sever liver damage may occur if

- adult takes more than 12 tablets in 24 hours
- child takes more than 5 tablets in 24 hours
- taken with other drugs containing acetaminophen
- adult has 3 or more alcoholic drinks everyday while using this product.

Do not use with any other drug containing acetaminophen (prescription or non prescription). If you are not sure whether a drug contains acetaminophen, ask a doctor or pharmacist.

Ask a doctor before use if the user has

- liver disease
- a breathing problem such as emphysema or chronic bronchitis
- glaucoma
- trouble urinating due to an enlarged prostate gland

Ask a doctor or pharmacist before use if the user is

- taking the blood thinning drug warfarin
- taking sedatives or tranquilizers

When using this product

- excitability may occur, especially in children
- drowsiness may occur
- avoid alcoholic beverages
- alcohol, sedatives and tranquilizers may increase drowsiness
- use caution when driving a motor vehicle or operating machinery

Stop use and ask a doctor if

- pain gets worse or lasts more than 5 days (children 6 to under 12 years) or 10 days (adults)
- fever gets worse or lasts more than 3 days
- redness or swelling is present
- new symptoms occur

PREGNANCY OR BREAST FEEDING

If pregnant or breast-feeding, ask a health professional before use.

Keep out of reach of children.

Overdose Warning

Taking more than the recommended dose may cause liver damage. In case of overdose, get medical help or contact a Poison Control Center right away. Quick medical attention is critical for adults as well as children even if you do not notice any signs or symptoms.

Directions

- do not use more than directed (see overdose warning)

Adults and children 12 years and over | 2 tablets every 4 to 6 hours, not more than 12 tablets in 24 hours
Children 6 to under 12 years of age | 1 tablet every 4 to 6 hours, not more than 5 tablets in 24 hours
Children under 6 years of age | ask a doctor

Other information

- store between 20° to 25°C (68° to 77°F)

Inactive ingredients

corn starch, FD&C red No. 40 aluminum lake, lactose anhydrous, magnesium stearate, microcrystalline cellulose, polyethylene glycol, polyvinyl alcohol, povidone, talc, titanium dioxide

Questions or comments?

Call 1-800-317-2165

PRINCIPAL DISPLAY PANEL - 10 Tablet Carton

Coricidin®
HBP

Decongestant-free
COLD SYMPTOM RELIEF for people with
HIGH BLOOD PRESSURE

Chlorpheniramine - Antihistamine,
Acetaminophen - Pain Reliever/Fever Reducer
See New Warnings Information

COLD
& FLU

Relieves:

- Runny Nose
- Sneezing
- Body Aches
  and Pains
- Fever

10 TABLETS